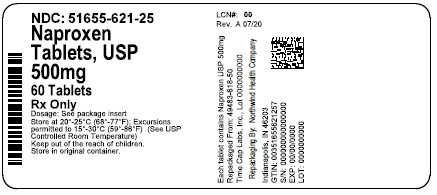 DRUG LABEL: NAPROXEN
NDC: 51655-621 | Form: TABLET
Manufacturer: Northwind Health Company, LLC
Category: prescription | Type: HUMAN PRESCRIPTION DRUG LABEL
Date: 20260101

ACTIVE INGREDIENTS: NAPROXEN 500 mg/1 1
INACTIVE INGREDIENTS: CROSCARMELLOSE SODIUM; MAGNESIUM STEARATE; POVIDONE

INDICATIONS AND USAGE

CAREFULLY CONSIDER THE POTENTIAL BENEFITS AND RISKS OF NAPROXEN AND OTHER TREATMENT OPTIONS BEFORE DECIDING TO USE NAPROXEN TABLETS. USE THE LOWEST EFFECTIVE DOSE FOR THE SHORTEST DURATION CONSISTENT WITH INDIVIDUAL PATIENT TREATMENT GOALS (SEE WARNINGS: GASTROINTESTINAL BLEEDING, ULCERATION, AND PERFORATION).

NAPROXEN TABLETS ARE INDICATED:

FOR THE RELIEF OF THE SIGNS AND SYMPTOMS OF RHEUMATOID ARTHRITIS.

FOR THE RELIEF OF THE SIGNS AND SYMPTOMS OF OSTEOARTHRITIS

FOR THE RELIEF OF THE SIGNS AND SYMPTOMS OF ANKYLOSING SPONDYLITIS

FOR THE RELIEF OF THE SIGNS AND SYMPTOMS OF JUVENILE ARTHRITIS

NAPROXEN TABLETS ARE ALSO INDICATED:

FOR RELIEF OF THE SIGNS AND SYMPTOMS OF TENDONITIS

FOR RELIEF OF THE SIGNS AND SYMPTOMS OF BURSITIS

FOR RELIEF OF THE SIGNS AND SYMPTOMS OF ACUTE GOUT

FOR THE MANAGEMENT OF PAIN

FOR THE MANAGEMENT OF PRIMARY DYSMENORRHEA

HOW SUPPLIED

NAPROXEN TABLETS

500 MG: WHITE TO OFF-WHITE, CAPSULE-SHAPED TABLETS WITH “140” DEBOSSED ON ONE SIDE AND SCORED ON

OTHER SIDE. PACKAGED IN LIGHT-RESISTANT BOTTLES OF 100 AND 500.

20'S (BOTTLE): NDC 51655-621-20

60’S (BOTTLE): NDC 51655-621-25

180’S (BOTTLE): NDC 51655-621-83

STORE AT 20°-25°C (68°-77°F) EXCURSIONS PERMITTED TO 15°-30°C (59°-86°F) IN WELL-CLOSED CONTAINERS

[SEE USP CONTROLLED ROOM TEMPERATURE]. DISPENSE IN LIGHT-RESISTANT CONTAINERS.

RX ONLY

WARNINGS

CARDIOVAS CULAR THROMBOTIC EVENTS

CLINICAL TRIALS OF SEVERAL COX-2 SELECTIVE AND NON-SELECTIVE NSAIDS OF UP TO THREE YEARS DURATION HAVE SHOWN AN INCREASED RISK OF SERIOUS CARDIOVASCULAR (CV) THROMBOTIC EVENTS, MYOCARDIAL INFARCTION, AND STROKE, WHICH CAN BE FATAL. BASED ON AVAILABLE DATA, IT IS UNCLEAR THAT THE RISK FOR CV THROMBOTIC EVENTS IS SIMILAR FOR ALL NSAIDS. THE RELATIVE INCREASE IN SERIOUS CV THROMBOTIC EVENTS OVER BASELINE CONFERRED BY NSAID USE APPEARS TO BE SIMILAR IN THOSE WITH AND WITHOUT KNOWN CV DISEASE OR RISK FACTORS FOR CV DISEASE. HOWEVER, PATIENTS WITH KNOWN CV DISEASE OR RISK FACTORS HAD A HIGHER ABSOLUTE INCIDENCE OF EXCESS SERIOUS CV THROMBOTIC EVENTS, DUE TO THEIR INCREASED BASELINE RATE. SOMEOBSERVATIONAL STUDIES FOUND THAT THIS INCREASED RISK OF SERIOUS CV THROMBOTIC EVENTS BEGAN AS EARLY AS THE FIRST WEEKS OF TREATMENT. THE INCREASE IN CV THROMBOTIC RISK HAS BEEN OBSERVED MOST CONSISTENTLY AT HIGHER DOSES.

TO MINIMIZE THE POTENTIAL RISK FOR AN ADVERSE CV EVENT IN NSAID-TREATED PATIENTS, USE THE LOWEST EFFECTIVE DOSE FOR THE SHORTEST DURATION POSSIBLE. PHYSICIANS AND PATIENTS SHOULD REMAIN ALERT FOR THE DEVELOPMENT OF SUCH EVENTS, THROUGHOUT THE ENTIRE TREATMENT COURSE, EVEN IN THE ABSENCE OF PREVIOUS CV SYMPTOMS. PATIENTS SHOULD BE INFORMED ABOUT THE SYMPTOMS OF SERIOUS CV EVENTS AND THE STEPS TO TAKE IF THEY OCCUR.

THERE IS NO CONSISTENT EVIDENCE THAT CONCURRENT USE OF ASPIRIN MITIGATES THE INCREASED RISK OF SERIOUS CV THROMBOTIC EVENTS ASSOCIATED WITH NSAID USE. THE CONCURRENT USE OF ASPIRIN AND AN NSAID, SUCH AS NAPROXEN, INCREASES THE RISK OF SERIOUS GASTROINTESTINAL (GI) EVENTS (SEE WARNINGS; GASTROINTESTINAL BLEEDING, ULCERATION, AND PERFORATION).

STATUS POST CORONARY ARTERY BYPASS GRAFT (CABG) SURGERY

TWO LARGE, CONTROLLED, CLINICAL TRIALS OF A COX-2 SELECTIVE NSAID FOR THE TREATMENT OF PAIN IN THE FIRST 10-14 DAYS FOLLOWING CABG SURGERY FOUND AN INCREASED INCIDENCE OF MYOCARDIAL INFARCTION AND STROKE. NSAIDS ARE CONTRAINDICATED IN THE SETTING OF CABG (SEE CONTRAINDICATIONS).

POST-MI PATIENTS

OBSERVATIONAL STUDIES CONDUCTED IN THE DANISH NATIONAL REGISTRY HAVE DEMONSTRATED THAT PATIENTS TREATED WITH NSAIDS IN THE POST-MI PERIOD WERE AT INCREASED RISK OF REINFARCTION, CV-RELATED DEATH, AND ALL CAUSE MORTALITY BEGINNING IN THE FIRST WEEK OF TREATMENT. IN THIS SAME COHORT, THE INCIDENCE OF DEATH IN THE FIRST YEAR POST-MI WAS 20 PER 100 PERSON YEARS IN NSAID-TREATED PATIENTS COMPARED TO 12 PER 100 PERSON YEARS IN NON-NSAID EXPOSED PATIENTS. ALTHOUGH THE ABSOLUTE RATE OF DEATH DECLINED SOMEWHAT

AFTER THE FIRST YEAR POST-MI, THE INCREASED RELATIVE RISK OF DEATH IN NSAID USERS PERSISTED OVER AT LEAST THE NEXT FOUR YEARS OF FOLLOW-UP.

AVOID THE USE OF NAPROXEN IN PATIENTS WITH A RECENT MI UNLESS THE BENEFITS ARE EXPECTED TO OUTWEIGH THE RISK OF RECURRENT CV THROMBOTIC EVENTS. IF NAPROXEN IS USED IN PATIENTS WITH A RECENT MI, MONITOR PATIENTS FOR SIGNS OF CARDIAC ISCHEMIA.

GASTROINTESTINAL BLEEDING, ULCERATION, AND PERFORATION

NSAIDS, INCLUDING NAPROXEN CAUSE SERIOUS GASTROINTESTINAL (GI) ADVERSE EVENTS INCLUDING INFLAMMATION, BLEEDING, ULCERATION, AND PERFORATION OF THE ESOPHAGUS, STOMACH, SMALL INTESTINE, OR LARGE INTESTINE, WHICH CAN BE FATAL. THESE SERIOUS ADVERSE EVENTS CAN OCCUR AT ANY TIME, WITH OR WITHOUT WARNING SYMPTOMS, IN PATIENTS TREATED WITH NSAIDS. ONLY ONE IN FIVE PATIENTS WHO DEVELOP A SERIOUS UPPER GI ADVERSE EVENT ON NSAID THERAPY IS SYMPTOMATIC. UPPER GI ULCERS, GROSS BLEEDING, OR PERFORATION CAUSED BY NSAIDS OCCURRED IN APPROXIMATELY 1% OF PATIENTS TREATED FOR 3-6 MONTHS, AND IN ABOUT 2%-

4% OF PATIENTS TREATED FOR ONE YEAR. HOWEVER, EVEN SHORT-TERM NSAID THERAPY IS NOT WITHOUT RISK. RISK FACTORS FOR GI BLEEDING, ULCERATION, AND PERFORATION PATIENTS WITH A PRIOR HISTORY OF PEPTIC ULCER DISEASE AND/OR GI BLEEDING WHO USED NSAIDS HAD A GREATER

THAN 10-FOLD INCREASED RISK FOR DEVELOPING A GI BLEED COMPARED TO PATIENTS WITHOUT THESE RISK FACTORS. OTHER FACTORS THAT INCREASE THE RISK OF GI BLEEDING IN PATIENTS TREATED WITH NSAIDS INCLUDE LONGER DURATION OF NSAID THERAPY; CONCOMITANT USE OF ORAL CORTICOSTEROIDS, ASPIRIN, ANTICOAGULANTS, OR SELECTIVE SEROTONIN REUPTAKE INHIBITORS (SSRIS); SMOKING; USE OF ALCOHOL; OLDER AGE; AND POOR GENERAL HEALTH STATUS. MOST POSTMARKETING REPORTS OF FATAL GI EVENTS OCCURRED IN ELDERLY OR DEBILITATED PATIENTS.

ADDITIONALLY, PATIENTS WITH ADVANCED LIVER DISEASE AND/OR COAGULOPATHY ARE AT INCREASED RISK FOR GI BLEEDING.

STRATEGIES TO MINIMIZE THE GI RISKS IN NSAID-TREATED PATIENTS:

- USE THE LOWEST EFFECTIVE DOSAGE FOR THE SHORTEST POSSIBLE DURATION.
- AVOID ADMINISTRATION OF MORE THAN ONE NSAID AT A TIME.
- AVOID USE IN PATIENTS AT HIGHER RISK UNLESS BENEFITS ARE EXPECTED TO OUTWEIGH THE INCREASED RISK OF
- BLEEDING. FOR SUCH PATIENTS, AS WELL AS THOSE WITH ACTIVE GI BLEEDING, CONSIDER ALTERNATE THERAPIES OTHER THAN NSAIDS.
- REMAIN ALERT FOR SIGNS AND SYMPTOMS OF GI ULCERATION AND BLEEDING DURING NSAID THERAPY.
- IF A SERIOUS GI ADVERSE EVENT IS SUSPECTED, PROMPTLY INITIATE EVALUATION AND TREATMENT, AND DISCONTINUE NAPROXEN UNTIL A SERIOUS GI ADVERSE EVENT IS RULED OUT.
- IN THE SETTING OF CONCOMITANT USE OF LOW-DOSE ASPIRIN FOR CARDIAC PROPHYLAXIS, MONITOR PATIENTS MORE CLOSELY FOR EVIDENCE OF GI BLEEDING (SEE PRECAUTIONS; DRUG INTERACTIONS).

HEPATOTOXICITY

ELEVATIONS OF ALT OR AST (THREE OR MORE TIMES THE UPPER LIMIT OF NORMAL [ULN]) HAVE BEEN REPORTED IN APPROXIMATELY 1% OF PATIENTS IN CLINICAL TRIALS. IN ADDITION, RARE, SOMETIMES FATAL, CASES OF SEVERE HEPATIC INJURY, INCLUDING FULMINANT HEPATITIS, LIVER NECROSIS AND HEPATIC FAILURE HAVE BEEN REPORTED.

ELEVATIONS OF ALT OR AST (LESS THAN THREE TIMES ULN) MAY OCCUR IN UP TO 15% OF PATIENTS TAKING NSAIDS INCLUDING NAPROXEN.

INFORM PATIENTS OF THE WARNING SIGNS AND SYMPTOMS OF HEPATOTOXICITY (E.G., NAUSEA, FATIGUE, LETHARGY, DIARRHEA, PRURITUS, JAUNDICE, RIGHT UPPER QUADRANT TENDERNESS, AND "FLULIKE" SYMPTOMS). IF CLINICAL SIGNS AND SYMPTOMS CONSISTENT WITH LIVER DISEASE DEVELOP, OR IF SYSTEMIC MANIFESTATIONS OCCUR (E.G., EOSINOPHILIA, RASH, ETC.), DISCONTINUE NAPROXEN IMMEDIATELY, AND PERFORM A CLINICAL EVALUATION OF THE PATIENT.

HYPERTENSION

NSAIDS, INCLUDING NAPROXEN, CAN LEAD TO ONSET OF NEW HYPERTENSION OR WORSENING OF PRE-EXISTING HYPERTENSION, EITHER OF WHICH MAY CONTRIBUTE TO THE INCREASED INCIDENCE OF CV EVENTS. PATIENTS TAKING ANGIOTENSIN CONVERTING ENZYME (ACE) INHIBITORS, THIAZIDES OR LOOP DIURETICS MAY HAVE IMPAIRED RESPONSE TO THESE THERAPIES WHEN TAKING NSAIDS (SEE PRECAUTIONS; DRUG INTERACTIONS).

MONITOR BLOOD PRESSURE (BP) DURING THE INITIATION OF NSAID TREATMENT AND THROUGHOUT THE COURSE OF THERAPY.

HEART FAILURE AND EDEMA

THE COXIB AND TRADITIONAL NSAID TRIALISTS’ COLLABORATION META-ANALYSIS OF RANDOMIZED CONTROLLED TRIALS DEMONSTRATED AN APPROXIMATELY TWO-FOLD INCREASE IN HOSPITALIZATION FOR HEART FAILURE IN COX-2 SELECTIVE-TREATED PATIENTS AND NONSELECTIVE NSAID-TREATED PATIENTS COMPARED TO PLACEBO-TREATED PATIENTS. IN A DANISH NATIONAL REGISTRY STUDY OF PATIENTS WITH HEART FAILURE, NSAID USE INCREASED THE RISK OF MI, HOSPITALIZATION FOR HEART FAILURE, AND DEATH. ADDITIONALLY, FLUID RETENTION AND EDEMA HAVE BEEN OBSERVED IN SOME PATIENTS TREATED WITH NSAIDS. USE OF NAPROXEN MAY BLUNT THE CV EFFECTS OF SEVERAL THERAPEUTIC AGENTS USED TO TREAT THESE MEDICAL CONDITIONS (E.G., DIURETICS, ACE INHIBITORS, OR ANGIOTENSIN RECEPTOR BLOCKERS [ARBS]) (SEE PRECAUTIONS; DRUG INTERACTIONS).

AVOID THE USE OF NAPROXEN IN PATIENTS WITH SEVERE HEART FAILURE UNLESS THE BENEFITS ARE EXPECTED TO OUTWEIGH THE RISK OF WORSENING HEART FAILURE. IF NAPROXEN IS USED IN PATIENTS WITH SEVERE HEART FAILURE, MONITOR PATIENTS FOR SIGNS OF WORSENING HEART FAILURE.

RENAL TOXICITY AND HYPERKALEMIA

RENAL TOXICITY

LONG-TERM ADMINISTRATION OF NSAIDS HAS RESULTED IN RENAL PAPILLARY NECROSIS AND OTHER RENAL INJURY.

RENAL TOXICITY HAS ALSO BEEN SEEN IN PATIENTS IN WHOM RENAL PROSTAGLANDINS HAVE A COMPENSATORY ROLE IN THE MAINTENANCE OF RENAL PERFUSION. IN THESE PATIENTS, ADMINISTRATION OF AN NSAID MAY CAUSE A DOSEDEPENDENT REDUCTION IN PROSTAGLANDIN FORMATION AND, SECONDARILY, IN RENAL BLOOD FLOW, WHICH MAY PRECIPITATE OVERT RENAL DECOMPENSATION. PATIENTS AT GREATEST RISK OF THIS REACTION ARE THOSE WITH IMPAIRED

RENAL FUNCTION, HYPOVOLEMIA, HEART FAILURE, LIVER DYSFUNCTION, SALT DEPLETION, THOSE TAKING DIURETICS AND ACE INHIBITORS OR ARBS, AND THE ELDERLY. DISCONTINUATION OF NSAID THERAPY IS USUALLY FOLLOWED BY RECOVERY TO THE PRETREATMENT STATE. NO INFORMATION IS AVAILABLE FROM CONTROLLED CLINICAL STUDIES REGARDING THE USE OF NAPROXEN IN PATIENTS WITH ADVANCED RENAL DISEASE. THE RENAL EFFECTS OF NAPROXEN MAY HASTEN THE PROGRESSION OF RENAL DYSFUNCTION IN PATIENTS WITH PREEXISTING RENAL DISEASE.

CORRECT VOLUME STATUS IN DEHYDRATED OR HYPOVOLEMIC PATIENTS PRIOR TO INITIATING NAPROXEN. MONITOR RENAL FUNCTION IN PATIENTS WITH RENAL OR HEPATIC IMPAIRMENT, HEART FAILURE, DEHYDRATION, OR HYPOVOLEMIA DURING USE OF NAPROXEN (SEE PRECAUTIONS; DRUG INTERACTIONS). AVOID THE USE OF NAPROXEN IN PATIENTS WITH ADVANCED RENAL DISEASE UNLESS THE BENEFITS ARE EXPECTED TO OUTWEIGH THE RISK OF WORSENING RENAL FUNCTION. IF NAPROXEN IS USED IN PATIENTS WITH ADVANCED RENAL DISEASE, MONITOR PATIENTS FOR SIGNS OF

WORSENING RENAL FUNCTION.

HYPERKALEMIA

INCREASES IN SERUM POTASSIUM CONCENTRATION, INCLUDING HYPERKALEMIA, HAVE BEEN REPORTED WITH USE OF NSAIDS, EVEN IN SOME PATIENTS WITHOUT RENAL IMPAIRMENT. IN PATIENTS WITH NORMAL RENAL FUNCTION, THESE EFFECTS HAVE BEEN ATTRIBUTED TO A HYPORENINEMIC HYPOALDOSTERONISM STATE.

ANAPHYLACTOID REACTIONS

NAPROXEN HAS BEEN ASSOCIATED WITH ANAPHYLACTIC REACTIONS IN PATIENTS WITH AND WITHOUT KNOWN HYPERSENSITIVITY TO NAPROXEN AND IN PATIENTS WITH ASPIRIN-SENSITIVE ASTHMA (SEE

CONTRAINDICATIONS, WARNINGS; EXACERBATION OF ASTHMA RELATED TO ASPIRIN SENSITIVITY).

EXACERBATION OF ASTHMA RELATED TO ASPIRIN SENSITIVITY

A SUBPOPULATION OF PATIENTS WITH ASTHMA MAY HAVE ASPIRIN-SENSITIVE ASTHMA WHICH MAY INCLUDE CHRONIC RHINOSINUSITIS COMPLICATED BY NASAL POLYPS; SEVERE, POTENTIALLY FATAL BRONCHOSPASM; AND/OR INTOLERANCE TO ASPIRIN AND OTHER NSAIDS. BECAUSE CROSS-REACTIVITY BETWEEN ASPIRIN AND OTHER NSAIDS HAS BEEN REPORTED IN SUCH ASPIRIN-SENSITIVE PATIENTS, NAPROXEN TABLETS ARE CONTRAINDICATED IN PATIENTS WITH THIS FORM OF ASPIRIN SENSITIVITY (SEE CONTRAINDICATIONS). WHEN NAPROXEN TABLETS ARE USED IN PATIENTS WITH PREEXISTING ASTHMA (WITHOUT KNOWN ASPIRIN SENSITIVITY), MONITOR PATIENTS FOR CHANGES IN THE SIGNS AND SYMPTOMS OF ASTHMA.

SERIOUS SKIN REACTIONS

NSAIDS, INCLUDING NAPROXEN, CAN CAUSE SERIOUS SKIN ADVERSE EVENTS SUCH AS EXFOLIATIVE DERMATITIS, STEVENS- JOHNSON SYNDROME (SJS), AND TOXIC EPIDERMAL NECROLYSIS (TEN), WHICH CAN BE FATAL. THESE SERIOUS EVENTS MAY OCCUR WITHOUT WARNING. PATIENTS SHOULD BE INFORMED ABOUT THE SIGNS AND SYMPTOMS OF SERIOUS SKIN MANIFESTATIONS AND TO DISCONTINUE THE USE OF NAPROXEN AT THE FIRST APPEARANCE OF SKIN RASH OR ANY OTHER SIGN OF HYPERSENSITIVITY. NAPROXEN TABLETS ARE CONTRAINDICATED IN PATIENTS WITH PREVIOUS

SERIOUS SKIN REACTIONS TO NSAIDS (SEE CONTRAINDICATIONS).

PREMATURE CLOSURE OF FETAL DUCTUS ARTERIOSUS

NAPROXEN MAY CAUSE PREMATURE CLOSURE OF THE FETAL DUCTUS ARTERIOSUS. AVOID USE OF NSAIDS, INCLUDING NAPROXEN, IN PREGNANT WOMEN STARTING AT 30 WEEKS OF GESTATION (THIRD TRIMESTER) (SEE PRECAUTIONS; PREGNANCY).

HEMATOLOGIC TOXICITY

ANEMIA HAS OCCURRED IN NSAID-TREATED PATIENTS. THIS MAY BE DUE TO OCCULT OR GROSS BLOOD LOSS, FLUID RETENTION, OR AN INCOMPLETELY DESCRIBED EFFECT ON ERYTHROPOIESIS. IF A PATIENT TREATED WITH NAPROXEN HAS ANY SIGNS OR SYMPTOMS OF ANEMIA, MONITOR HEMOGLOBIN OR HEMATOCRIT.

NSAIDS, INCLUDING NAPROXEN, MAY INCREASE THE RISK OF BLEEDING EVENTS. CO-MORBID CONDITIONS SUCH AS COAGULATION DISORDERS, OR CONCOMITANT USE OF WARFARIN AND OTHER ANTICOAGULANTS, ANTIPLATELET AGENTS (E.G., ASPIRIN), SEROTONIN REUPTAKE INHIBITORS (SSRIS) AND SEROTONIN NOREPINEPHRINE REUPTAKE INHIBITORS (SNRIS) MAY INCREASE THIS RISK. MONITOR THESE PATIENTS FOR SIGNS OF BLEEDING (SEE PRECAUTIONS; DRUG

INTERACTIONS).

DOSAGE AND ADMINISTRATION

CAREFULLY CONSIDER THE POTENTIAL BENEFITS AND RISKS OF NAPROXEN AND OTHER TREATMENT OPTIONS BEFORE DECIDING TO USE NAPROXEN TABLETS. USE THE LOWEST EFFECTIVE DOSE FOR THE SHORTEST DURATION CONSISTENT WITH INDIVIDUAL PATIENT TREATMENT GOALS (SEE WARNINGS; GASTROINTESTINAL BLEEDING, ULCERATION, AND PERFORATION).

AFTER OBSERVING THE RESPONSE TO INITIAL THERAPY WITH NAPROXEN TABLETS, THE DOSE AND FREQUENCY SHOULD BE ADJUSTED TO SUIT AN INDIVIDUAL PATIENT'S NEEDS.

DIFFERENT DOSE STRENGTHS AND FORMULATIONS (I.E., TABLETS, SUSPENSION) OF THE DRUG ARE NOT NECESSARILY BIOEQUIVALENT. THIS DIFFERENCE SHOULD BE TAKEN INTO CONSIDERATION WHEN CHANGING FORMULATION.

ALTHOUGH NAPROXEN TABLETS, NAPROXEN SUSPENSION, NAPROXEN DELAYED-RELEASED TABLETS, AND NAPROXEN SODIUM TABLETS ALL CIRCULATE IN THE PLASMA AS NAPROXEN, THEY HAVE PHARMACOKINETIC DIFFERENCES THAT MAY AFFECT ONSET OF ACTION. ONSET OF PAIN RELIEF CAN BEGIN WITHIN 1 HOUR IN PATIENTS TAKING NAPROXEN. THE RECOMMENDED STRATEGY FOR INITIATING THERAPY IS TO CHOOSE A FORMULATION AND A STARTING DOSE LIKELY TO BE EFFECTIVE FOR THE PATIENT AND THEN ADJUST THE DOSAGE BASED ON OBSERVATION OF BENEFIT AND/OR ADVERSE EVENTS. A LOWER DOSE SHOULD BE CONSIDERED IN PATIENTS WITH RENAL OR HEPATIC IMPAIRMENT OR IN ELDERLY PATIENTS (SEE WARNINGS; HEPATOTOXICITY, AND RENAL TOXICITY AND HYPERKALEMIA, AND PRECAUTIONS; GERIATRIC USE).

GERIATRIC PATIENTS

STUDIES INDICATE THAT ALTHOUGH TOTAL PLASMA CONCENTRATION OF NAPROXEN IS UNCHANGED, THE UNBOUND PLASMA FRACTION OF NAPROXEN IS INCREASED IN THE ELDERLY. CAUTION IS ADVISED WHEN HIGH DOSES ARE REQUIRED AND SOME ADJUSTMENT OF DOSAGE MAY BE REQUIRED IN ELDERLY PATIENTS. AS WITH OTHER DRUGS USED IN THE ELDERLY, IT IS PRUDENT TO USE THE LOWEST EFFECTIVE DOSE.

PATIENTS WITH MODERATE TO SEVERE RENAL IMPAIRMENT

NAPROXEN-CONTAINING PRODUCTS ARE NOT RECOMMENDED FOR USE IN PATIENTS WITH MODERATE TO SEVERE AND SEVERE RENAL IMPAIRMENT (CREATININE CLEARANCE < 30 ML/MIN) (SEE WARNINGS: RENAL EFFECTS).

RHEUMATOID ARTHRITIS, OSTEOARTHRITIS AND ANKYLOSING SPONDYLITIS

THE RECOMMENDED DOSE IS 250 MG, 375 MG, OR 500 MG TWICE DAILY. DURING LONG-TERM ADMINISTRATION, THE DOSE OF NAPROXEN MAY BE ADJUSTED UP OR DOWN DEPENDING ON THE CLINICAL RESPONSE OF THE PATIENT. A LOWER DAILY DOSE MAY SUFFICE FOR LONG-TERM ADMINISTRATION. THE MORNING AND EVENING DOSES DO NOT HAVE TO BE EQUAL IN SIZE AND THE ADMINISTRATION OF THE DRUG MORE FREQUENTLY THAN TWICE DAILY IS NOT NECESSARY. IN PATIENTS WHO TOLERATE LOWER DOSES WELL, THE DOSE MAY BE INCREASED TO NAPROXEN 1500 MG/DAY FOR LIMITED PERIODS OF UP TO 6 MONTHS WHEN A HIGHER LEVEL OF ANTI-INFLAMMATORY/ANALGESIC ACTIVITY IS REQUIRED. WHEN TREATING SUCH PATIENTS WITH NAPROXEN 1500 MG/DAY, THE PHYSICIAN SHOULD OBSERVE SUFFICIENT INCREASED CLINICAL BENEFITS TO OFFSET THE POTENTIAL INCREASED RISK. THE MORNING AND EVENING DOSES DO NOT HAVE TO BE EQUAL IN SIZE AND ADMINISTRATION OF THE DRUG MORE FREQUENTLY THAN TWICE DAILY DOES NOT GENERALLY MAKE A DIFFERENCE IN RESPONSE (SEE CLINICAL PHARMACOLOGY).

JUVENILE ARTHRITIS

NAPROXEN TABLETS MAY NOT ALLOW FOR THE FLEXIBLE DOSE TITRATION NEEDED IN PEDIATRIC PATIENTS WITH JUVENILE ARTHRITIS. A LIQUID FORMULATION MAY BE MORE APPROPRIATE. IN PEDIATRIC PATIENTS, DOSES OF 5 MG/KG/DAY PRODUCED PLASMA LEVELS OF NAPROXEN SIMILAR TO THOSE SEEN IN ADULTS TAKING 500 MG OF NAPROXEN (SEE CLINICAL PHARMACOLOGY). THE RECOMMENDED TOTAL DAILY DOSE OF NAPROXEN IS APPROXIMATELY 10 MG/KG GIVEN IN 2 DIVIDED DOSES. ONE-HALF OF THE 250 MG TABLET WILL BE NEEDED FOR DOSING LOWER-WEIGHT CHILDREN. DOSING WITH NAPROXEN TABLETS IS NOT APPROPRIATE FOR CHILDREN WEIGHING LESS THAN 25 KILOGRAMS. THE RECOMMENDED TOTAL DAILY DOSE OF NAPROXEN IS APPROXIMATELY 10 MG/KG GIVEN IN 2 DIVIDED DOSES (I.E., 5 MG/KG GIVEN TWICE A DAY). NAPROXEN TABLETS ARE NOT WELL SUITED TO THIS DOSAGE SO USE OF NAPROXEN ORAL SUSPENSION IS RECOMMENDED FOR THIS INDICATION.

MANAGEMENT OF PAIN, PRIMARY DYSMENORRHEA, AND ACUTE TENDONITIS AND BURSITIS

BECAUSE THE SODIUM SALT OF NAPROXEN IS MORE RAPIDLY ABSORBED, NAPROXEN SODIUM IS RECOMMENDED FOR THE MANAGEMENT OF ACUTE PAINFUL CONDITIONS WHEN PROMPT ONSET OF PAIN RELIEF IS DESIRED. NAPROXEN MAY ALSO BE USED. THE RECOMMENDED STARTING DOSE OF NAPROXEN IS 500 MG, FOLLOWED BY 500 MG EVERY 12 HOURS OR 250 MG EVERY 6 TO 8 HOURS AS REQUIRED. THE INITIAL TOTAL DAILY DOSE SHOULD NOT EXCEED 1250 MG OF NAPROXEN.

ACUTE GOUT

THE RECOMMENDED STARTING DOSE IS 750 MG OF NAPROXEN FOLLOWED BY 250 MG EVERY 8 HOURS UNTIL THE ATTACK HAS SUBSIDED.

MED GUIDE FOR NAPROXEN TABLETS USP 250 MG 375 MG 500 MG

Medication Guide for Non-Steroidal Anti-Inflammatory Drugs (NSAIDs)

Medication Guide for Nonsteroidal Anti-Inflammatory Drugs (NSAIDs)

What is the most important information I should know about medicines called Non-Steroidal Anti-Inflammatory Drugs (NSAIDs)?
NSAIDs can cause serious side effects, including:

Increased risk of a heart attack or stroke that can lead to death. This risk may happen early in treatment and may increase:

o with increasing doses of NSAIDs
o with longer use of NSAIDs
Do not take NSAIDs right before or after a heart surgery called a “coronary artery bypass graft (CABG).”
Avoid taking NSAIDs after a recent heart attack, unless your healthcare provider tells you to. You may have an increased risk of another heart attack if you take NSAIDs after a recent heart attack.

Increased risk of bleeding, ulcers, and tears (perforation) of the esophagus (tube leading from the mouth to the stomach), stomach and intestines:

o any time during use
o without warning symptoms
o that may cause death
The risk of getting an ulcer or bleeding increases with:
o past history of stomach ulcers, or stomach or intestinal bleeding with use of NSAIDs
o taking medicines called “corticosteroids”, “anticoagulants”, “SSRIs”, or “SNRIs”
o increasing doses of NSAIDs o older age
o longer use of NSAIDs o poor health
o smoking o advanced liver disease
o drinking alcohol o bleeding problems
NSAIDs should only be used:
o exactly as prescribed
o at the lowest dose possible for your treatment
o for the shortest time needed

What are NSAIDs?
NSAIDs are used to treat pain and redness, swelling, and heat (inflammation) from medical conditions such as different types of arthritis, menstrual cramps, and other types of short-term pain.

Who should not take NSAIDs?
Do not take NSAIDs:
• if you have had an asthma attack, hives, or other allergic reaction with aspirin or any other NSAIDs.
• right before or after heart bypass surgery.

Before taking NSAIDs, tell your healthcare provider about all of your medical conditions, including if you:
• have liver or kidney problems
• have high blood pressure
• have asthma
• are pregnant or plan to become pregnant. Talk to your healthcare provider if you are considering taking NSAIDs during pregnancy. You should not take NSAIDs after 29 weeks of pregnancy.
• are breastfeeding or plan to breastfeed.
Tell your healthcare provider about all of the medicines you take, including prescription or over-the-counter medicines, vitamins or herbal supplements. NSAIDs and some other medicines can interact with each other and cause serious side effects. Do not start taking any new medicine without talking to your healthcare provider first.

What are the possible side effects of NSAIDs?
NSAIDs can cause serious side effects, including:
See “What is the most important information I should know about medicines called Nonsteroidal Anti-inflammatory Drugs (NSAIDs)"?
• new or worse high blood pressure
• heart failure
• liver problems including liver failure
• kidney problems including kidney failure
• low red blood cells (anemia)
• life-threatening skin reactions
• life-threatening allergic reactions
• Other side effects of NSAIDs include: stomach pain, constipation, diarrhea, gas, heartburn, nausea, vomiting, and dizziness.
Get emergency help right away if you have any of the following symptoms:

shortness of breath or trouble breathing
chest pain
weakness in one part or side of your body
slurred speech
swelling of the face or throat

Stop taking your NSAID and call your healthcare provider right away if you get any of the following symptoms:

nausea
more tired or weaker than usual
diarrhea
itching
your skin or eyes look yellow
indigestion or stomach pain
flu-like symptoms
vomit blood
there is blood in your bowel movement or it is black and sticky like tar
unusual weight gain
skin rash or blisters with fever
swelling of the arms and legs, hands and feet

If you take too much of your NSAID, call your healthcare provider or get medical help right away.
These are not all the possible side effects of NSAIDs. For more information, ask your healthcare provider or pharmacist about NSAIDs. Call your doctor for medical advice about side effects. You may report side effects to Marksans at 1-877-376-4271 and/orFDA at 1-800-FDA-1088.

Other information about NSAIDs

Aspirin is an NSAID medicine but it does not increase the chance of a heart attack. Aspirin can cause bleeding in the brain, stomach, and intestines. Aspirin can also cause ulcers in the stomach and intestines.
Some NSAIDs are sold in lower doses without a prescription (over-the-counter). Talk to your healthcare provider before using over-the-counter NSAIDs for more than 10 days.

General information about the safe and effective use of NSAIDs
Medicines are sometimes prescribed for purposes other than those listed in a Medication Guide. Do not use NSAIDs for a condition for which it was not prescribed. Do not give NSAIDs to other people, even if they have the same symptoms that you have. It may harm them.
If you would like more information about NSAIDs, talk with your healthcare provider. You can ask your pharmacist or healthcare provider for information about NSAIDs that is written for health professionals.

Manufactured for:
Time-Cap Labs, Inc.
7 Michael Avenue,
Farmingdale,
NY 11735, USA
Manufactured by:
Marksans Pharma Ltd.
Plot No. L-82, L-83,
Verna Indl. Estate,
Verna, GOA - 403722, India.

This Medication Guide has been approved by the U.S. Food and Drug Administration.

Revised: October 2017

Principal Display Panel

NDC: 51655-621-25